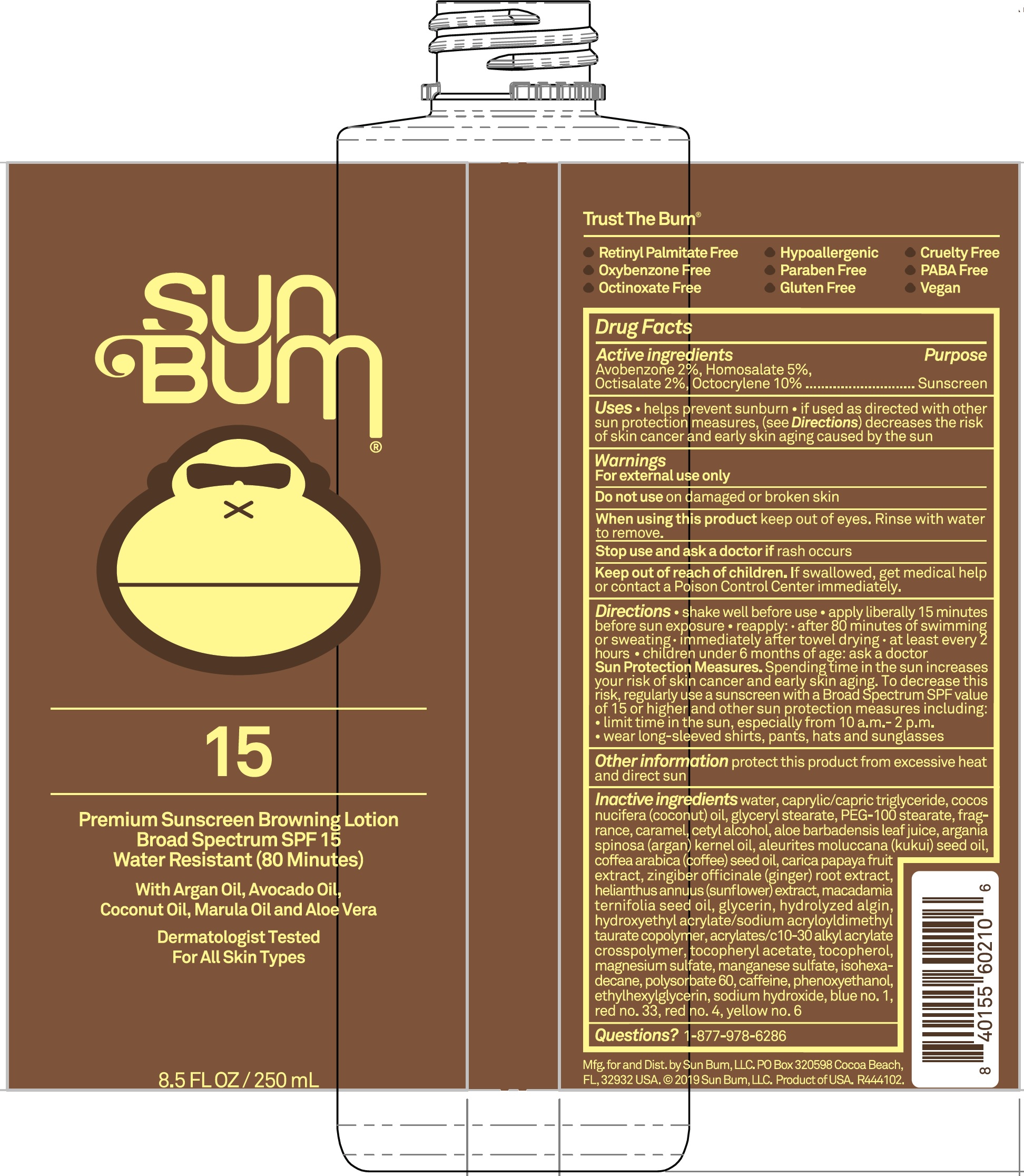 DRUG LABEL: Sun Bum Premium Sunscreen Browning SPF 15
NDC: 69039-643 | Form: LOTION
Manufacturer: Sun Bum LLC
Category: otc | Type: HUMAN OTC DRUG LABEL
Date: 20220204

ACTIVE INGREDIENTS: AVOBENZONE 20 mg/1 mL; HOMOSALATE 50 mg/1 mL; OCTISALATE 20 mg/1 mL; OCTOCRYLENE 100 mg/1 mL
INACTIVE INGREDIENTS: FD&C RED NO. 4; D&C RED NO. 33; FD&C YELLOW NO. 6; PAPAYA JUICE; GLYCERYL MONOSTEARATE; WATER; MEDIUM-CHAIN TRIGLYCERIDES; COCONUT OIL; PEG-100 STEARATE; CARAMEL; CETYL ALCOHOL; ALOE VERA LEAF; ARGAN OIL; KUKUI NUT; ARABICA COFFEE OIL; GINGER; HELIANTHUS ANNUUS FLOWERING TOP; MACADAMIA OIL; GLYCERIN; HYDROXYETHYL ACRYLATE/SODIUM ACRYLOYLDIMETHYL TAURATE COPOLYMER (100000 MPA.S AT 1.5%); .ALPHA.-TOCOPHEROL ACETATE; TOCOPHEROL; MAGNESIUM SULFATE, UNSPECIFIED FORM; MANGANESE SULFATE; ISOHEXADECANE; POLYSORBATE 60; CAFFEINE; PHENOXYETHANOL; ETHYLHEXYLGLYCERIN; SODIUM HYDROXIDE; FD&C BLUE NO. 1; CARBOMER INTERPOLYMER TYPE A (ALLYL SUCROSE CROSSLINKED); SODIUM ALGINATE

Sun Bum Premium Sunscreen Browning Lotion SPF 15

Active ingredients

Avobenzone 2%, Homosalte 5%,
Octisalate 2%, Octocrylene 10%

Purpose

Sunscreen

Uses

- helps prevent sunburn
- if used as directed with other sun protection measures, (see Directions) decreases the risk of skin cancer and early skin aging caused by the sun

Warnings

For external use only

Do not use

on damaged or broken skin

When using this product

keep out of eyes. Rinse with water to remove.

Stop use and ask a doctor if

rash occurs

Keep out of reach of children.

If swallowed, get medical help or contact a Poison Control Center immediately.

Directions

• shake well before use • apply liberally 15 minutes before sun exposure • reapply: • after 80 minutes of swimming or sweating • immediately after towel drying • at least every 2 hours • children under 6 months of age: ask a doctor

Sun Protection Measures. Spending time in the sun increases your risk of skin cancer and early skin aging. To decrease this risk, regularly use a sunscreen with a Broad Spectrum SPF value of 15 or higher and other sun protection measures including:

- limit time in the sun, especially from 10 a.m.-2 p.m.
- wear long-sleeved shirts, pants, hats and sunglasses

Other information

protect this product from excessive heat and direct sun

Inactive ingredients

water, caprylic/capric triglyceride, cocos nucifera (coconut) oil, glyceryl stearate, PEG-100 stearate, fragrance, caramel, cetyl alcohol, aloe barbadensis leaf juice, argania spinosa (argan) kernel oil, aleurites moluccana (kukui) seed oil, coffea arabica (coffee) seed oil, caprica papaya fruit extract, zingiber officinale (ginger) root extract, helianthus annuus (sunflower) extract, macadamia ternifolia seed oil, glycerin, hydrolyzed algin, hydroxyethyl acrylate/sodium acryloyldimethyl taurate copolymer, acrylate/c 10-30 alkyl acrylate crosspolymer, tocopheryl acetate, tocopherol, magnesium sulfate, manganese sulfate, isohexadecane, polysorbate 60, caffeine, phenoxyethanol, ethylhexylglycerin, sodium hydroxide, blue no.1, red no.33, red no.4, yellow no.6

Questions?

1-877-978-6286